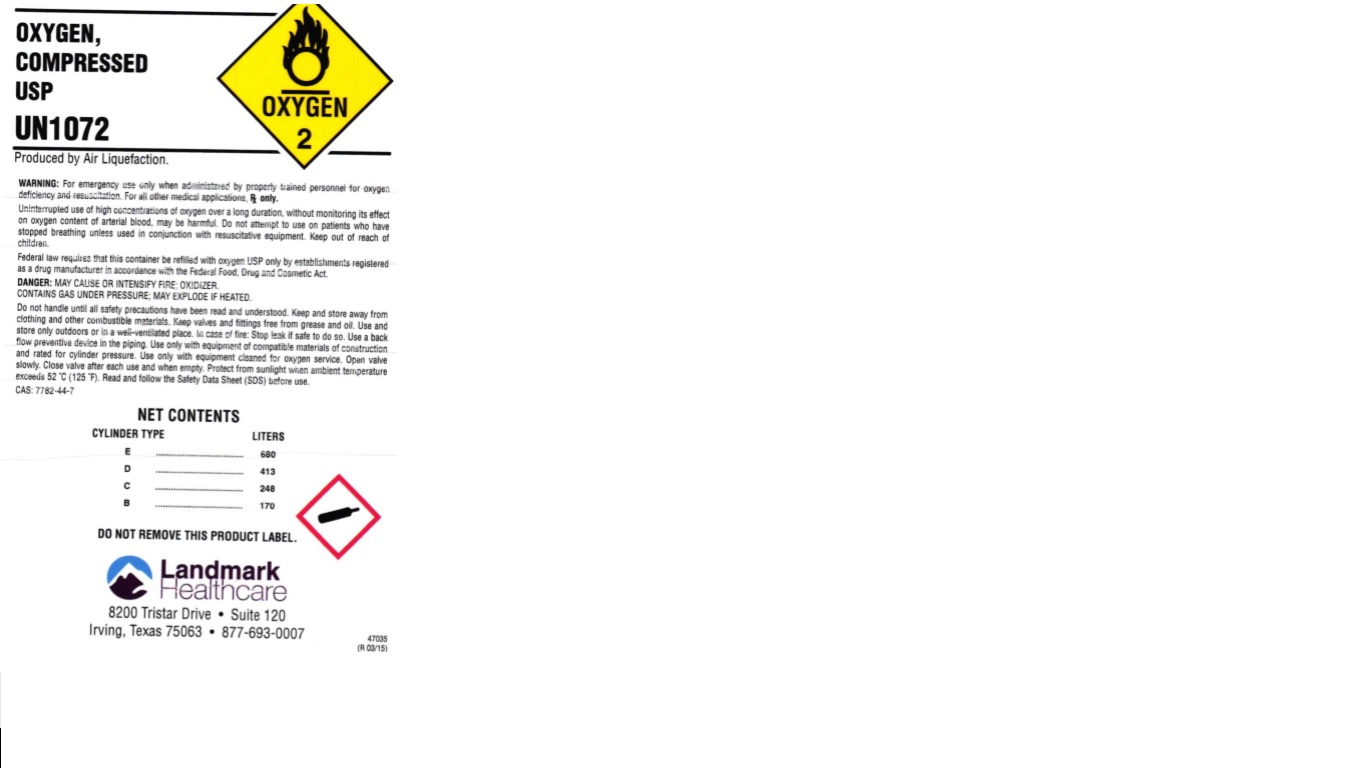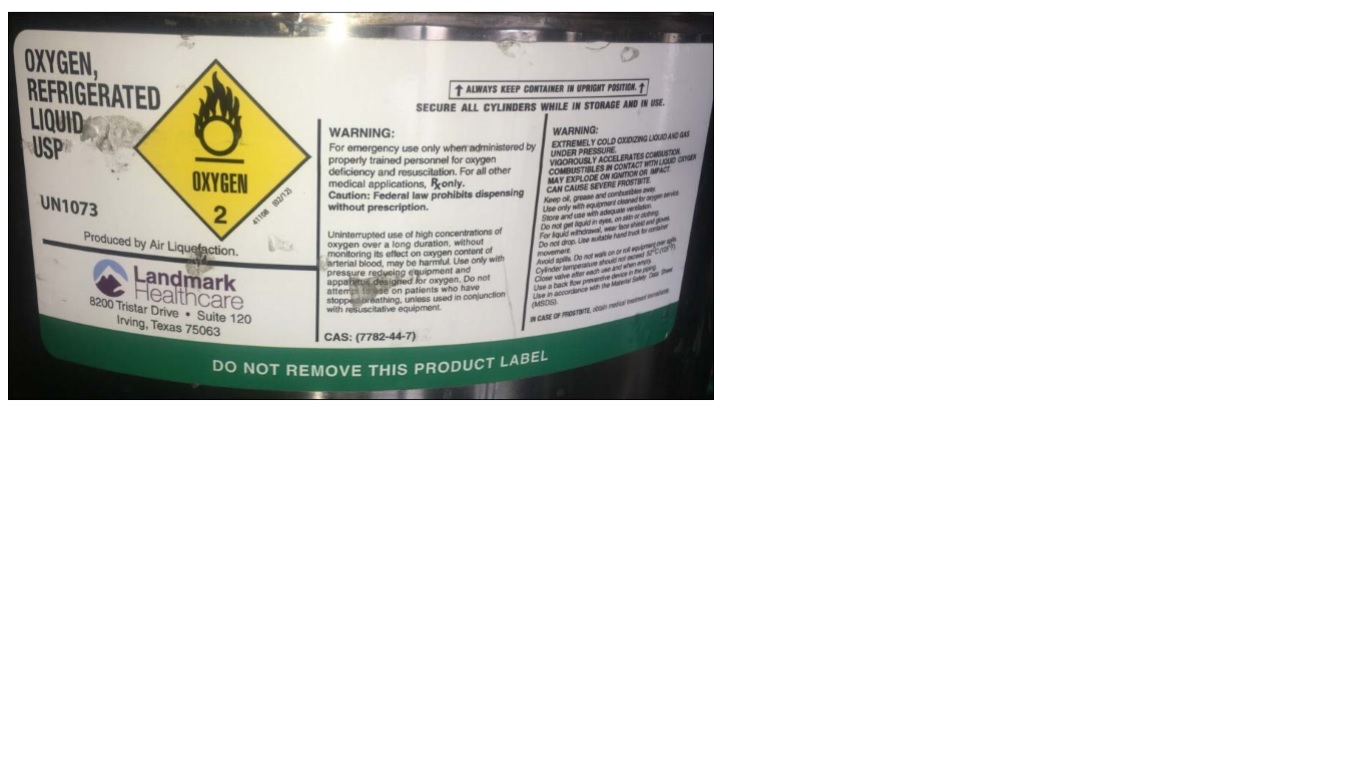 DRUG LABEL: Oxygen
NDC: 29149-001 | Form: GAS
Manufacturer: Landmark Healthcare, Inc.
Category: prescription | Type: HUMAN PRESCRIPTION DRUG LABEL
Date: 20241107

ACTIVE INGREDIENTS: OXYGEN 990 mL/1 L

oxygen

PACKAGE LABEL

OXYGEN, COMPRESSED USP UN1072

Produced by Air Liquefication

OXYGEN 2

WARNING: For emergency use only when administered by properly trained personnel for oxygen

deficiency and resuscitation. For all other applications, Rx only.

Uninterrupted use of high concentrations of oxygen over a long duration, without monitoring its effect

on oxygen content of arterial blood, may be harmful. Do not attempt to use on patients who have stopped breathing, unless used in conjunction with resuscitative equipment. Keep out of reach of children.

Federal law requires that this container be refilled with oxygen USP only by establishments registered as a drug manufacturer in accordance with the Federal Food, Drug and Cosmetic Act.

DANGER: MAY CAUSE OR INTENSIFY FIRE; OXIDIZER CONTAINS GAS UNDER PRESSURE; MAY EXPLODE IF HEATED.

Do not handle until all safety precautions have been read and understood. Keep and store away from clothing and combustible materials. Keep valves and fittings free from grease and oil. Use and store only outdoors or in a well-ventilated place. In case of fire: Stop leak if safe to do so. Use a back flow preventive device in the piping. Use only with equipment compatible materials of construction and rated for cylinder pressure. Use only with equipment cleaned for oxygen service. Open valve slowly. Close valve after each use and when empty. Protect from sunlight when ambient temperature exceeds 52 C (125 F). Read and follow the Safety Data Sheet (SDS) before use.

CAS: 7782-44-7

NET CONTENTS

CYLINDER TYPES LITERS

E 680

D 413

C 248

B 170

DO NOT REMOVE THIS PRODUCT LABEL.

LANDMARK HEALTHCARE

8200 Tristar Drive, Suite 120 Irving, Texas 75063 877-693-0007

PACKAGE LABEL

OXYGEN REFRIGERATED LIQUID, USP UN1073

Produced by Air Liquefication

OXYGEN 2

ALWAYS KEEP CONTAINER IN UPRIGHT POSITION.

SECURE ALL CYLINDERS WHILE IN STORAGE AND IN USE.

WARNING:

For emergency use only when administered by properly trained personnel for oxygen deficiency and

resuscitation. For all other medical applications, Rx only.

Caution: Federal Law Prohibits Dispensing without Prescription.

Uninterrupted use of high concentrations of oxygen over a long duration, without monitoring its effect

on oxygen content of arterial blood, may be harmful. Use only with pressure reducing equipment and

apparatus designed for oxygen. Do not attempt to use on patients who have stopped breathing, unless

used in conjunction with resuscitative equipment.

CAS: (7782-44-7)

WARNING:

EXTREMELY COLD OXIDIZING LIQUID AND GAS UNDER PRESSURE.

VIGOROUSLY ACCELERATES COMBUSTION. COMBUSTIBLES IN CONTACT WITH LIQUID

OXYGEN MAY EXPLODE ON IGNITION OR IMPACT. CAN CAUSE SEVERE FROSTBITE.

Keep oil, grease and combustibles away. Use only with equipment cleaned for oxygen service. Store and use with adequate ventilation. Do not get liquid in eyes, on skin, or clothing. For liquid withdrawal, use face shield and gloves. Do not drop. Use suitable hand truck for container movement.

Avoid spills. Do not walk on or roll equipment over spills. Close valve after each use and when empty. Use in accordance with the Material Safety Data Sheet (MSDS).

IN CASE OF FROST BITE, obtain medical treatment immediately.

DO NOT REMOVE THIS PRODUCT LABEL

LANDMARK HEALTHCARE

8200 Tristar Drive, Suite 120 Irving, Texas 75063 877-693-0007